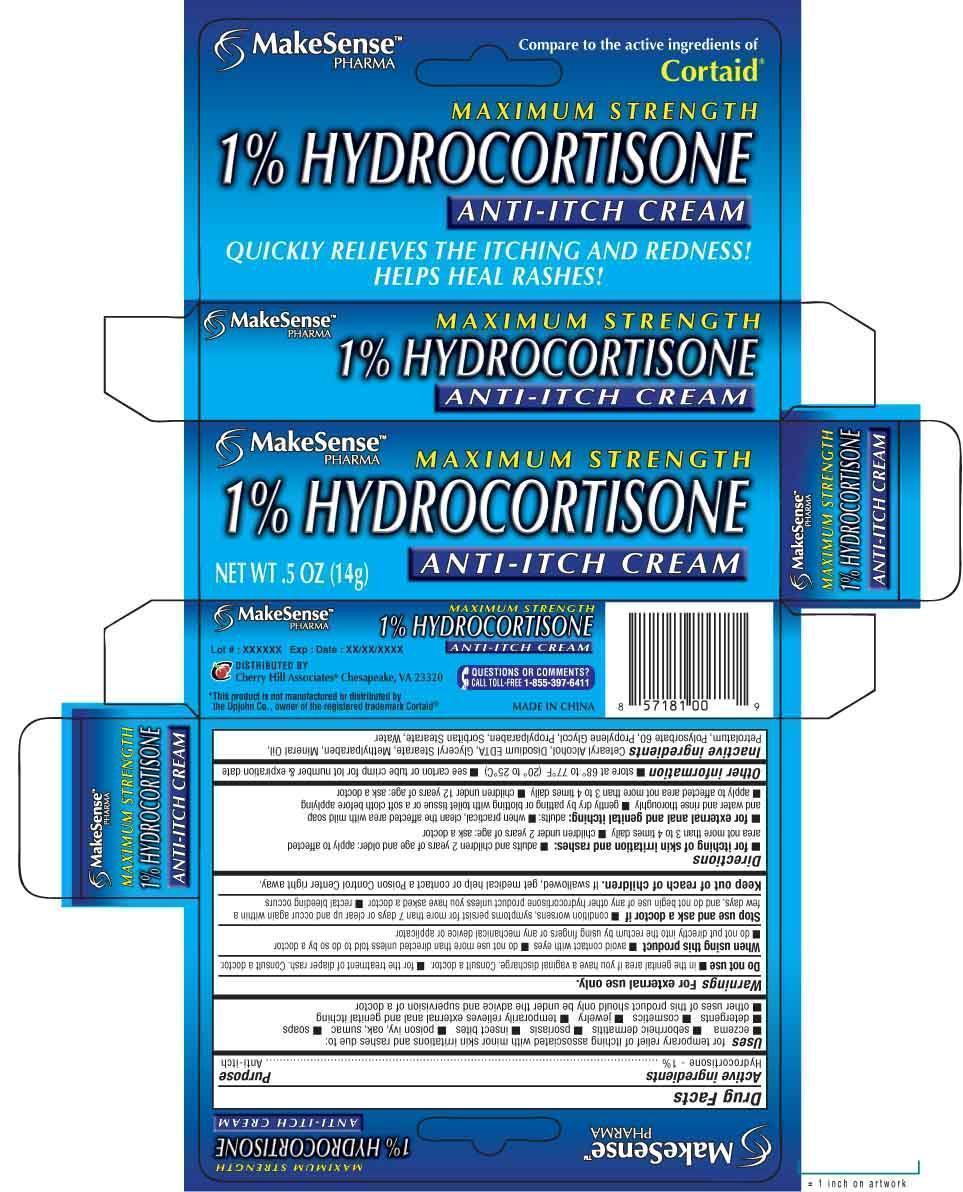 DRUG LABEL: MAKESENSE
NDC: 69020-204 | Form: CREAM
Manufacturer: Cherry Hill Sales Co
Category: otc | Type: HUMAN OTC DRUG LABEL
Date: 20160808

ACTIVE INGREDIENTS: HYDROCORTISONE 1 g/100 g
INACTIVE INGREDIENTS: CETOSTEARYL ALCOHOL; EDETATE DISODIUM; GLYCERYL STEARATE SE; METHYLPARABEN; MINERAL OIL; PETROLATUM; POLYSORBATE 60; PROPYLENE GLYCOL; PROPYLPARABEN; SORBITAN MONOSTEARATE; WATER

Drug Facts

Active Ingredient

Hydrocortisone 1%

Purpose

Anti-itch

Uses

■ for temporary relief of itching associated with minor skin irritations and rashes due to: ■ eczema ■ seborrheic dermatitis ■ psoriasis ■insect bites ■ poison ivy, oak, sumac ■ soaps ■ detergents ■ cosmetics ■ jewelry ■ temporarily relieves external anal and genital itching ■ other uses of this product should be under the advice and supervision of a doctor

Warnings

For external use only

Do not use

■ in the genital area if you have vaginal discharge. Consult a doctor ■ for the treatment of diaper rash. Consult a doctor

When using this product

■ avoid contact with eyes ■ do not use more than directed unless told to do so by a doctor ■ do not put directly into the rectum by using fingers or any mechanical device or applicator

Stop use and ask a doctor if

■ the condition worsens, symptoms persist for more than 7 days or clear up and occur again wihin a few days, and do not beginuse of any other hydrocortisone product unless you have asked a doctor ■ rectal bleed occurs

Keep out of reach of children

If swallowed, get medical help or contact a Poison Control Center right away

Directions

■ for itching of skin irritation and rashes: ■ adults and children 2 years of age and older: apply to affected
area not more than 3 to 4 times daily ■ children under 2 years of age: ask a doctor

for external anal and genital itching: adults: ■ when practical, clean the affected area with mild soap and water and rinse thoroughly ■ gently dry by patting or blotting with toilet tissue or a soft cloth before applying ■ apply to affected area not more than 3 to 4 times daily ■ children under 12 years of age: ask a doctor

Other information

■ store at 68-77F (20 to 25C) ■ see carton or tube crimp for lot number and expiration date

Inactive Ingredients

Cetearyl Alcohol, Disodium EDTA, Glyceryl Stearate, Methylparaben, Mineral Oil, Petrolatum, Polysorbate 60, Propylene Glycol, Propylparaben, Sorbitan Stearate, Water